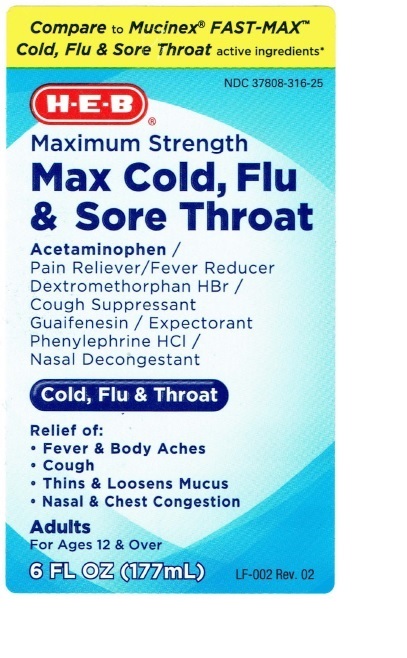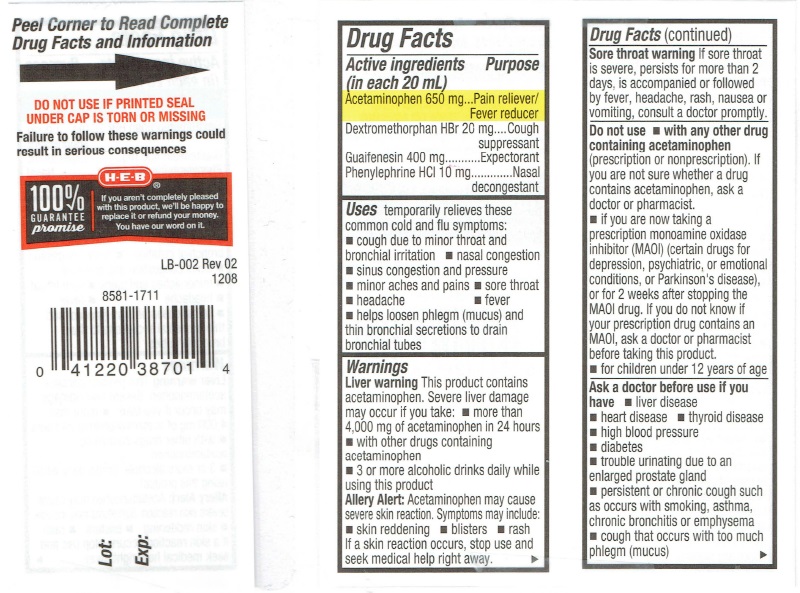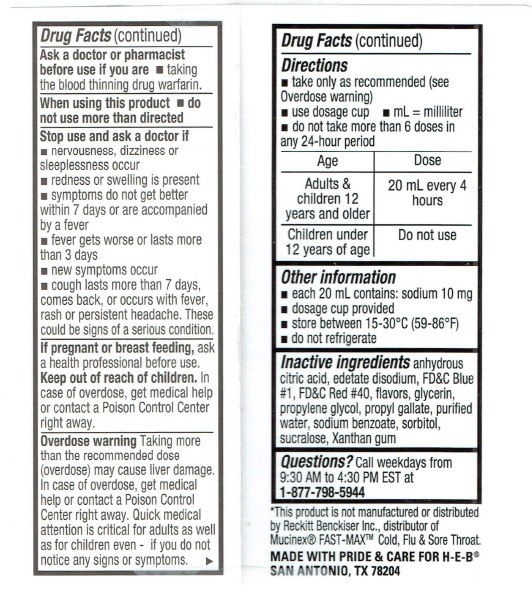 DRUG LABEL: MAX Cold, Flu, and Sore Throat
NDC: 37808-316 | Form: LIQUID
Manufacturer: H E B
Category: otc | Type: HUMAN OTC DRUG LABEL
Date: 20231229

ACTIVE INGREDIENTS: ACETAMINOPHEN 650 mg/20 mL; DEXTROMETHORPHAN HYDROBROMIDE 20 mg/20 mL; GUAIFENESIN 400 mg/20 mL; PHENYLEPHRINE HYDROCHLORIDE 10 mg/20 mL
INACTIVE INGREDIENTS: ANHYDROUS CITRIC ACID; EDETATE DISODIUM; FD&C BLUE NO. 1; FD&C RED NO. 40; GLYCERIN; PROPYLENE GLYCOL; PROPYL GALLATE; WATER; SODIUM BENZOATE; SORBITOL; SUCRALOSE; XANTHAN GUM

Drug Facts Active ingredients

Active ingredients (in each 20 mL)
Acetaminophen 650 mg
Dextromethorphan HBr 20 mg
Guaifenesin 400 mg
Phenylephrine HCL 10 mg

Purpose

Pain reliever/Fever reducer
Cough suppressant
Expectorant
Nasal Decongestant

Keep out of reach of children.

In case of overdose, get medical help or contact a Poison Control Center right awaay.

Uses

temporarily relieves these common cold and flu symptoms:

- cough due to minor throat and bronchial irritation
- nasal congestion
- sinus congestion and pressure
- minor aches and pains
- sore throat
- headache
- fever
- helps loosed phlegm (mucus) ang thin bronchial secretions to drain bronchial tubes

Warnings

Liver warning This product contains
acetaminophen. Severe liver damage
may occur if you take: ■ more than
4,000 mg of acetaminophen in 24 hours
■ with other drugs containing
acetaminophen
■ 3 or more alcoholic drinks daily while
using this product

Allery Alert: Acetaminophen may cause
severe skin reaction. Symptoms may include:
■ skin reddening - blisters ■ rash
If a skin reaction occurs, stop use and
seek medical help right away.

Sore throat warning If sore throat
is severe, persists for more than 2
days, is accompanied or followed
by fever, headache, rash, nausea or vomiting, consult a doctor promptly.

Do not use

- with any other drug containing acetaminophen (prescription or nonprescription). If you are not sure whether a drug contains acetaminophen, ask a doctor or pharmacist.
- if you are taking a prescription monamine oxidase inhibitor)MAOI) (certain drugs for depression, psychiatric, or emotional conditions, or Parkinson's disease), or for 2 weeks after stopping the MAOI drug. If you do not know if your prescription drug contains an MAOI, ask a doctor or pharmacist before taking this product
- for children under 12 years of age

Ask a doctor before use if you have

- liver disease
- heart disease
- thyroid disease
- high blood pressure
- diabetes
- trouble urinating due to an enlarged prostate gland
- persistent or chronic cough such as occurs with smoking, asthma or empysema
- cough that occurs with too much phlegm (mucus)

Ask a doctor or pharmacist before use if you are

- taking the blood thinning drug warfarin.

When using this product

- do not use more than directed

Stop use and ask a doctor if

- nervousness, dizziness or sleeplessness occur
- redness or swelling is present
- symptoms do not get better within 7 days or are accompanied by a fever
- fever gets worse or lasts more than 3 days
- new symptoms occur
- cough lasts more than 7 days, comes back, or occurs with fever, rash or persistent headache. These could be signs of a serious condition.

If pregnant or breast feeding

ask a health professional before use.

Overdose warning

Taking more than the recommended dose (overdose) may cause liver damage. In case of overdose, get medical help or contact the Poison Control Center right away. Quick medical attention is critical for adults as well as for children even if you do not notice any signs or symptoms.

Directions

Age Dose
Adults and children 12 years and older 20 mL every 4 hours

Children under 12 years of age Do not use

Other information

- each 20 mL contains: sodium 10 mg
- dosage cup provided
- store between 20°-25° C (68°-7°7 F)
- do not refrigerate

Inactive ingredients

Anhydrous citric acid, edetate disodium, FD and C Blue #1, FD and C Red #40, flavors, glycerin, propylene glycol, propyl gallate, purified water, sodium benzoate, sorbitol, sucralose, Xanthan gum

Questions?

Call weekdays from 9:30 AM to 4:30 PM EST at 1-877-798-5944

Product Label

Compare to Mucinex® FAST-MAX™

Cold, Flu & Sore Throat active ingredients*

NDC 37808-316-25

H E B®

Maximum Strength

MAX COLD, FLU & SORE THROAT

Acetaminophen /
(Pain Reliver/Fever Reducer)
Dextromethorphan HBr /
(Cough Suppressant)
Guaifensin / (Expectorant)
Phenylephrine HCL /
Nasal Decongestant)

Cold, Flu & Throat

Relief of:
• Fever and Body aches
• Controls Cough
• Thins and Loosens Mucus
• Relieves Nasal and Chest Congestion

Adults
For ages 12 and Over

6 FL OZ (117 mL) LF-002 Rev.2 02

Peel Corner to Read Complete Drug Facts and Information

DO NOT USE IF PRINTED SEAL UNDER CAP IS TORN OR MISSING
Failure to follow these warnings could result in consequences

100%
GUARANTEE
promise

If you aren't completely pleased
with this product, we’ll be happy to
replace it or refund your money.
You have our word on it.

LB-002 Rev 02

1208
Lot:
Exp: